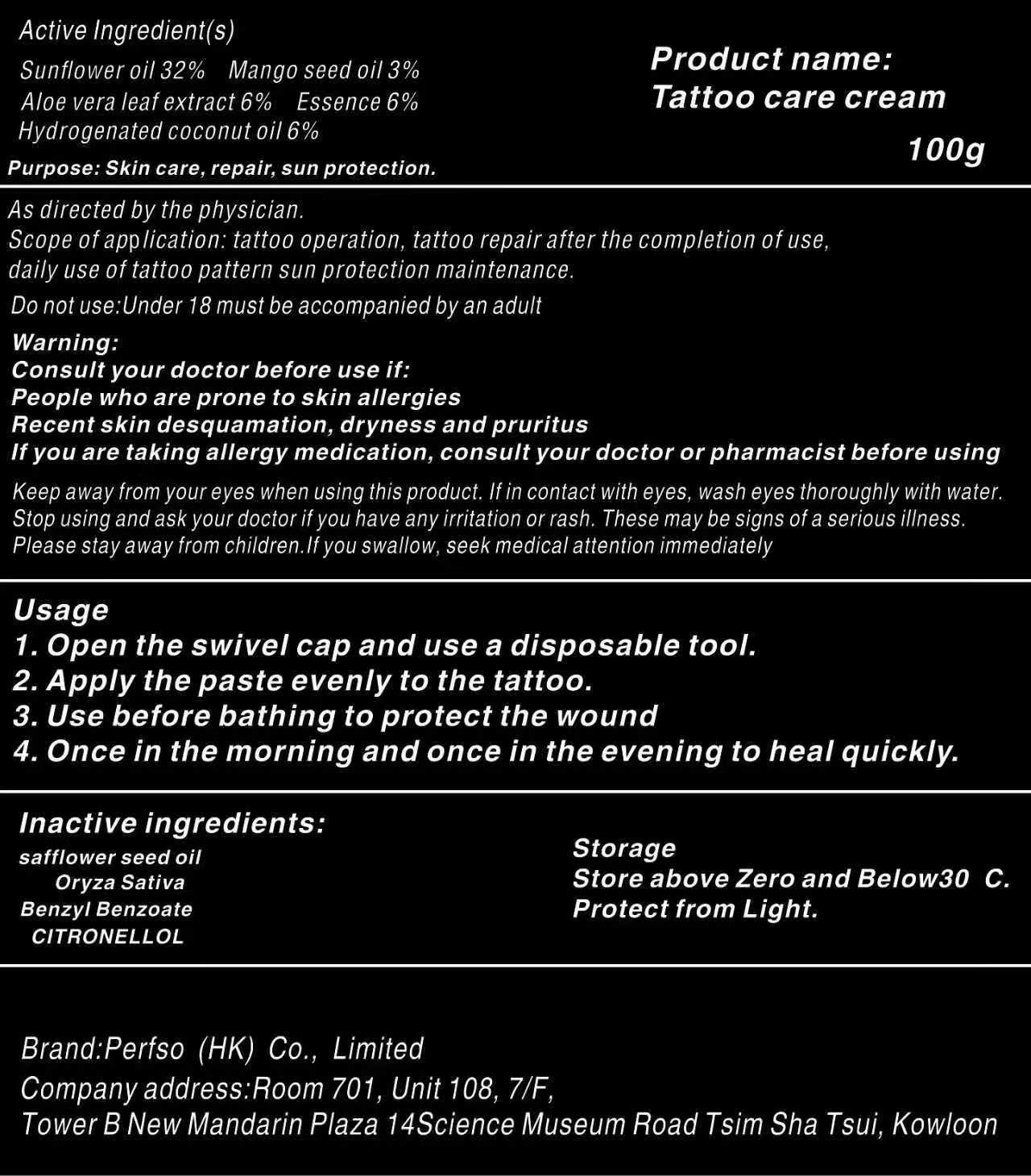 DRUG LABEL: Tattoo care
NDC: 85942-002 | Form: CREAM
Manufacturer: Perfso (HK) Co., Limited
Category: otc | Type: HUMAN OTC DRUG LABEL
Date: 20251104

ACTIVE INGREDIENTS: COSTUS ROOT OIL 6 g/100 g; ALOE VERA LEAF 6 g/100 g; SUNFLOWER OIL 32 g/100 g; MANGO SEED OIL 3 g/100 g; HYDROGENATED COCONUT OIL 6 g/100 g
INACTIVE INGREDIENTS: CITRONELLOL; RICE BRAN OIL; SAFFLOWER SEED OIL POLYGLYCERYL-6 ESTERS; BENZYL BENZOATE

ACTIVE INGREDIENT

Sunflower oil 32%, Mango seed oil 3%, Aloe vera leaf extract 6%, Essence 6%, Hydrogenated coconut oil 6%

PURPOSE

Skin care, repair, sun protection.

INDICATIONS AND USAGE

As directed by the physician.

Scope of application: tattoo operation, tattoo repair after the completion of use, daily use of tattoo pattern sun protection maintenance.

WARNINGS

Consult your doctor before use if:

People who are prone to skin allergies Recent skin desquamation, dryness and pruritus If you are taking allergy medication, consult your doctor or pharmacist before using

Do not use:Under 18 must be accompanied by an adult

WHEN USING

Keep away from your eyes when using this product. If in contact with eyes, wash eyes thoroughly with water.

STOP USE

Stop using and ask your doctor if you have any irritation or rash. These may be signs of a serious illness.

Please stay away from children.If you swallow, seek medical attention immediately

Keep out of reach for children.

DOSAGE AND ADMINISTRATION

Usage

1.Open the swivel cap and use a disposable tool.

2. Apply the paste evenly to the tattoo.

3.Use before bathing to protect the wound

4.Once in the morning and once in the evening to heal quickly.

Storage

Store above Zero and Below 30 C. Protect from Light.

INACTIVE INGREDIENT

safflower seed oil, Oryza Sativa, Benzyl Benzoate, CITRONELLOL